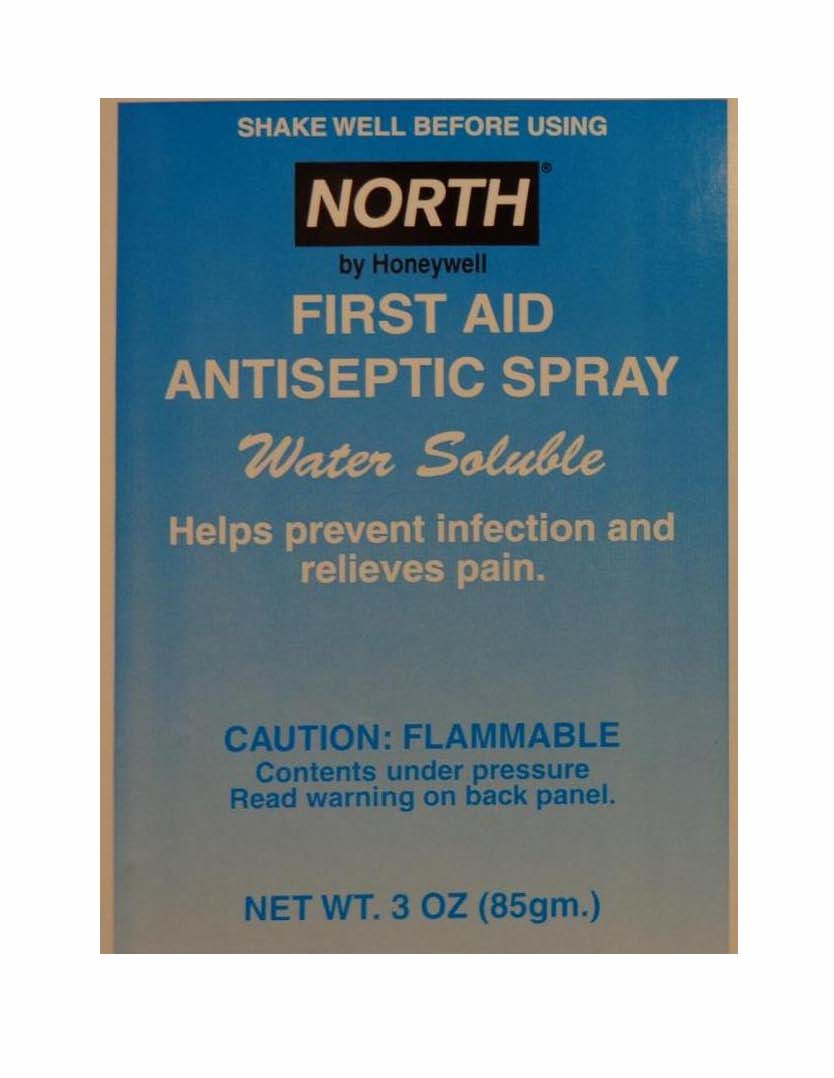 DRUG LABEL: North First Aid Antiseptic
                
NDC: 0498-0015 | Form: SPRAY
Manufacturer: North Safety Products
Category: otc | Type: HUMAN OTC DRUG LABEL
Date: 20130406

ACTIVE INGREDIENTS: BENZOCAINE 10 g/100 g; BENZETHONIUM CHLORIDE 0.2 g/100 g
INACTIVE INGREDIENTS: DIPROPYLENE GLYCOL; ISOBUTANE; BUTANE; PROPANE

North First Aid Antiseptic Spray

ACTIVE INGREDIENT

Benzethonium chloride 0.02% w/w

Benzocaine 10% w/w

Purpose

Topical antiseptic

Topical anesthetic

Uses

for temporary relief of pain and itching and helps protect against infection in:

- minor cuts and scrapes
- insect bites
- minor skin irritations

Warnings

For external use only

Flammable

- keep away from fire or flame
- contents under pressure
- do not puncture or incinerate container
- do not expose to temperatures above 120o F

Do not use

- in or near the eyes or other mucus membranes
- in case of serious burns
- in case of deep or puncture wounds
- for prolonged period of time
- on large portion of the body

Stop use and ask a doctor if

- condition worsens or symptoms persist for more than 7 days
- condition clears up and recurs within a few days
- redness, swelling or irritation occurs

Keep out of the reach of children

If swallowed, get medical help or contact a Poison Control Center right away

Directions

- clean the affected area
- shake can well before using
- hold 4 - 6 inches from surface and spray area until wet
- may be covered with a sterile bandage, if bandaged let dry first
- for adult institutional use only
- not intended for use on children

Other information

- avoid inhaling
- use only as directed
- intentional misuse by deliberately concentrating or inhaling the contents may be harmful or fatal

Inactive ingredients

dipropylene glycol, isobutane, n-butane, propane

Principal Display Panel

Enter section text here